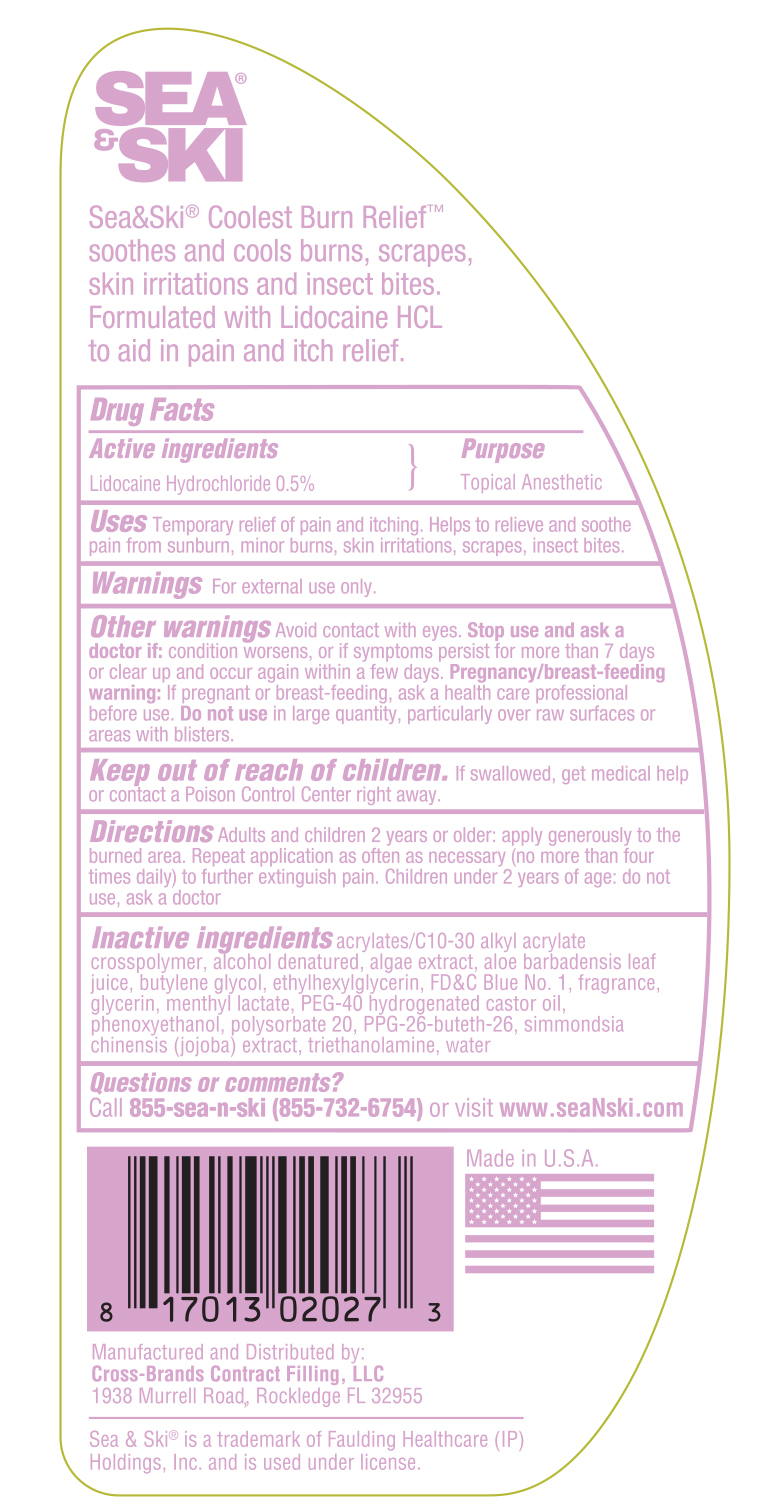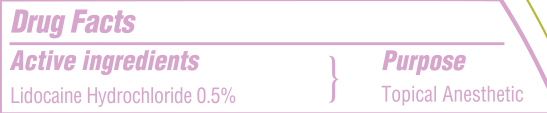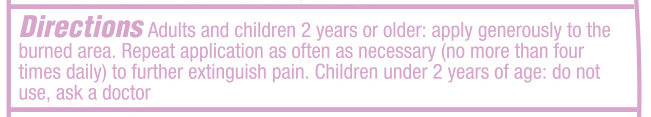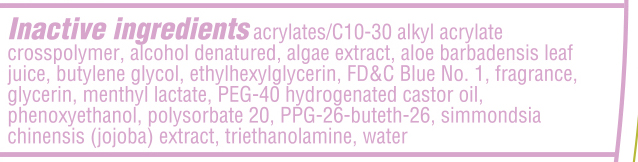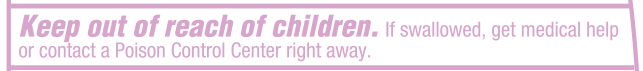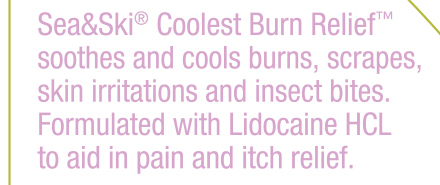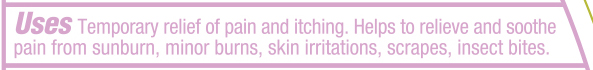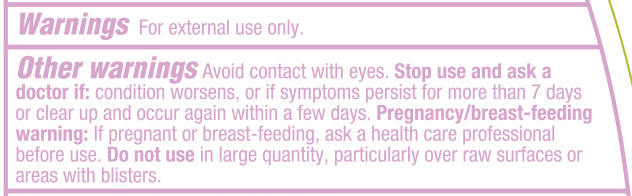 DRUG LABEL: Sea and Ski Coolest Burn Relief
NDC: 73440-2027 | Form: GEL
Manufacturer: Cross Brands Contract Filling
Category: otc | Type: HUMAN OTC DRUG LABEL
Date: 20210219

ACTIVE INGREDIENTS: LIDOCAINE HYDROCHLORIDE 11.9 g/234.6 g
INACTIVE INGREDIENTS: WATER 207.8 mL/234.6 g

Sea & Ski Coolest Burn Relief